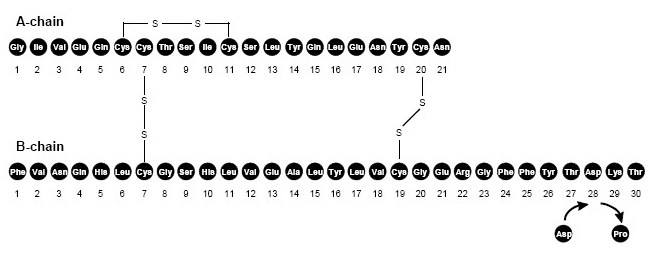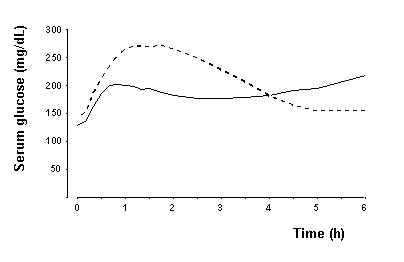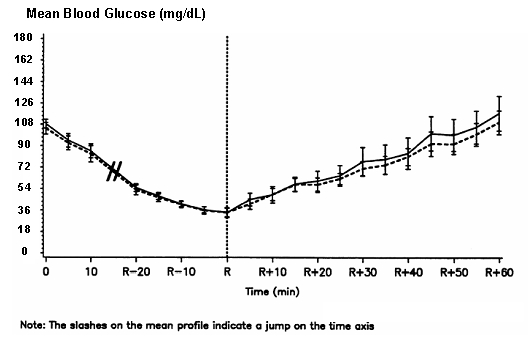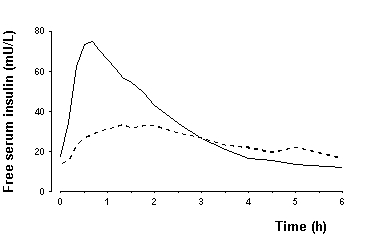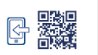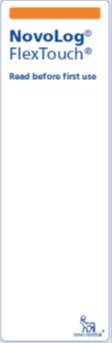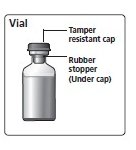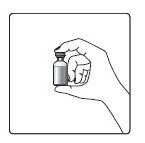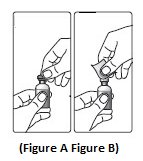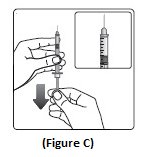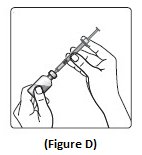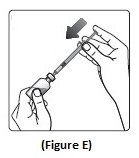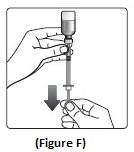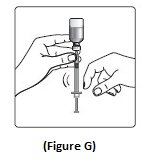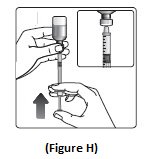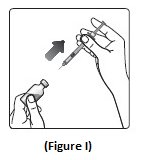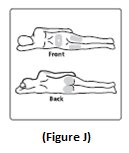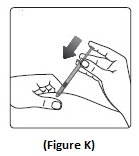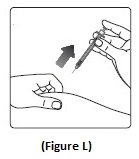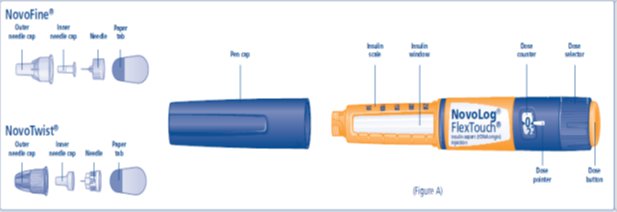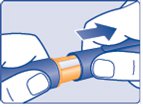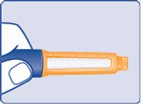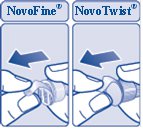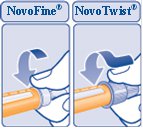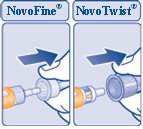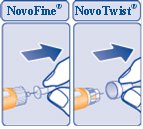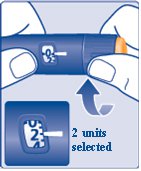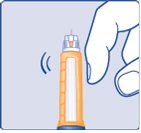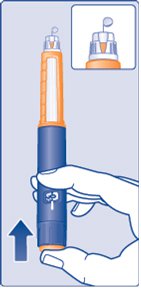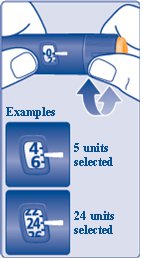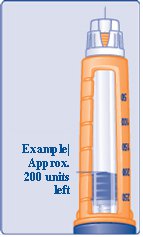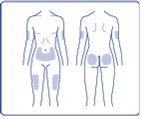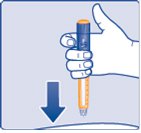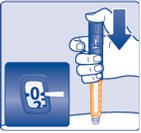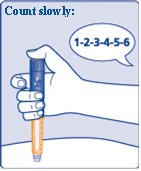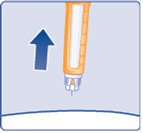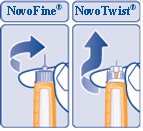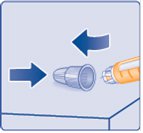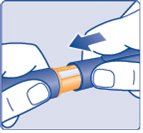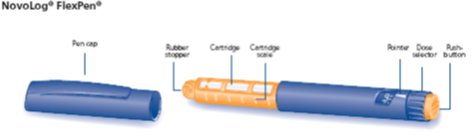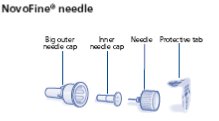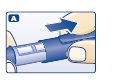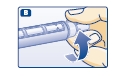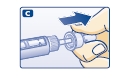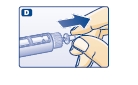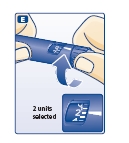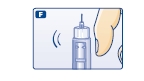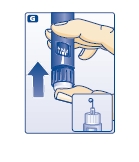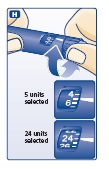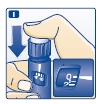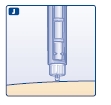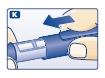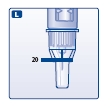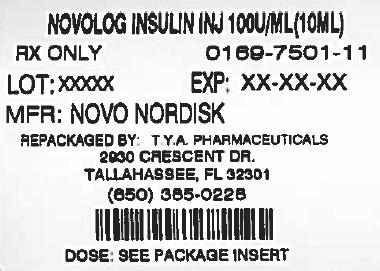 DRUG LABEL: NovoLog
NDC: 64725-0750 | Form: INJECTION, SOLUTION
Manufacturer: TYA Pharmaceuticals
Category: prescription | Type: HUMAN PRESCRIPTION DRUG LABEL
Date: 20140425

ACTIVE INGREDIENTS: INSULIN ASPART 100 [iU]/1 mL
INACTIVE INGREDIENTS: SODIUM PHOSPHATE, DIBASIC, DIHYDRATE 1.25 mg/1 mL; GLYCERIN 16 mg/1 mL; HYDROCHLORIC ACID; METACRESOL 1.72 mg/1 mL; PHENOL 1.5 mg/1 mL; SODIUM CHLORIDE 0.58 mg/1 mL; SODIUM HYDROXIDE; ZINC 19.6 ug/1 mL

HIGHLIGHTS OF PRESCRIBING INFORMATION

These highlights do not include all the information needed to use NovoLog safely and effectively. See full prescribing information for NovoLog. NovoLog (insulin aspart [rDNA origin] injection) solution for subcutaneous use Initial U.S. Approval: 2000
®

1 INDICATIONS AND USAGE

- NovoLog is an insulin analog indicated to improve glycemic control in adults and children with diabetes mellitus (). 1.1

2 DOSAGE AND ADMINISTRATION

- The dosage of NovoLog must be individualized.
- NovoLog should generally be given immediately (within 5-10 minutes) prior to the start of a meal (). Subcutaneous injection:2.2
- : Change the NovoLog in the reservoir at least every 6 days, change the infusion set, and the infusion set insertion site at least every 3 days. NovoLog should not be mixed with other insulins or with a diluent when it is used in the pump). Use in pumps (2.3
- : NovoLog should be used at concentrations from 0.05 U/mL to 1.0 U/mL insulin aspart in infusion systems using polypropylene infusion bags. NovoLog has been shown to be stable in infusion fluids such as 0.9% sodium chloride (). Intravenous use 2.4

3 DOSAGE FORMS AND STRENGTHS

Each presentation contains 100 Units of insulin aspart per mL (U-100)

- 10 mL vials () 3
- 3 mL PenFill cartridges for the 3 mL PenFill cartridge device () ® 3
- 3 mL NovoLog FlexPen () ® 3
- 3 mL NovoLog FlexTouch () ® 3

4 CONTRAINDICATIONS

- Do not use during episodes of hypoglycemia (). 4
- Do not use in patients with hypersensitivity to NovoLog or one of its excipients.

5 WARNINGS AND PRECAUTIONS

- Hypoglycemia is the most common adverse effect of insulin therapy. Glucose monitoring is recommended for all patients with diabetes. Any change of insulin dose should be made cautiously and only under medical supervision (,). 5.15.2
- Insulin, particularly when given intravenously or in settings of poor glycemic control, can cause hypokalemia. Use caution in patients predisposed to hypokalemia). (5.3
- Like all insulins, NovoLog requirements may be reduced in patients with renal impairment or hepatic impairment ,). (5.45.5
- Severe, life-threatening, generalized allergy, including anaphylaxis, may occur with insulin products, including NovoLog (). 5.6
- Fluid retention and heart failure can occur with concomitant use of thiazolidinediones (TZDs), which are PPAR-gamma agonists, and insulin, including NovoLog (). 5.10

6 ADVERSE REACTIONS

Adverse reactions observed with NovoLog include hypoglycemia, allergic reactions, local injection site reactions, lipodystrophy, rash and pruritus (). 6

To report SUSPECTED ADVERSE REACTIONS, contact Novo Nordisk Inc. at 1-800-727-6500 or FDA at 1-800-FDA-1088 or www.fda.gov/medwatch.

7 DRUG INTERACTIONS

- The following may increase the blood-glucose-lowering effect and susceptibility to hypoglycemia: oral antidiabetic products, pramlintide, ACE inhibitors, disopyramide, fibrates, fluoxetine, monoamine oxidase inhibitors, propoxyphene, salicylates, somatostatin analogs, sulfonamide antibiotics (). 7
- The following may reduce the blood-glucose-lowering effect: corticosteroids, niacin, danazol, diuretics, sympathomimetic agents (e.g., epinephrine, salbutamol, terbutaline), isoniazid, phenothiazine derivatives, somatropin, thyroid hormones, estrogens, progestogens (e.g., in oral contraceptives), atypical antipsychotics (). 7
- Beta-blockers, clonidine, lithium salts, and alcohol may either potentiate or weaken the blood-glucose-lowering effect of insulin (). 7
- Pentamidine may cause hypoglycemia, which may sometimes be followed by hyperglycemia (). 7
- The signs of hypoglycemia may be reduced or absent in patients taking sympatholytic products such as beta-blockers, clonidine, guanethidine, and reserpine (). 7

8 USE IN SPECIFIC POPULATIONS

- Pediatric: Has not been studied in children with type 2 diabetes. Has not been studied in children with type 1 diabetes <2 years of age (8.4).

FULL PRESCRIBING INFORMATION

1 INDICATIONS AND USAGE

1.1 Treatment of Diabetes Mellitus

NovoLog is an insulin analog indicated to improve glycemic control in adults and children with diabetes mellitus.

2 DOSAGE AND ADMINISTRATION

2.1 Dosing

NovoLog is an insulin analog with an earlier onset of action than regular human insulin. The dosage of NovoLog must be individualized. NovoLog given by subcutaneous injection should generally be used in regimens with an intermediate or long-acting insulin [ ]. The total daily insulin requirement may vary and is usually between 0.5 to 1.0 units/kg/day. When used in a meal-related subcutaneous injection treatment regimen, 50 to 70% of total insulin requirements may be provided by NovoLog and the remainder provided by an intermediate-acting or long-acting insulin. Because of NovoLog’s comparatively rapid onset and short duration of glucose lowering activity, some patients may require more basal insulin and more total insulin to prevent pre-meal hyperglycemia when using NovoLog than when using human regular insulin. see Warnings and Precautions (5), How Supplied/Storage and Handling (16.2)

Do not use NovoLog that is viscous (thickened) or cloudy; use only if it is clear and colorless. NovoLog should not be used after the printed expiration date.

2.2 Subcutaneous Injection

NovoLog should be administered by subcutaneous injection in the abdominal region, buttocks, thigh, or upper arm. Because NovoLog has a more rapid onset and a shorter duration of activity than human regular insulin, it should be injected immediately (within 5-10 minutes) before a meal. Injection sites should be rotated within the same region to reduce the risk of lipodystrophy. As with all insulins, the duration of action of NovoLog will vary according to the dose, injection site, blood flow, temperature, and level of physical activity.

NovoLog may be diluted with Insulin Diluting Medium for NovoLog for subcutaneous injection. Diluting one part NovoLog to nine parts diluent will yield a concentration one-tenth that of NovoLog (equivalent to U-10). Diluting one part NovoLog to one part diluent will yield a concentration one-half that of NovoLog (equivalent to U-50).

2.3 Continuous Subcutaneous Insulin Infusion (CSII) by External Pump

NovoLog can also be infused subcutaneously by an external insulin pump [see ]. Diluted insulin should not be used in external insulin pumps. Because NovoLog has a more rapid onset and a shorter duration of activity than human regular insulin, pre-meal boluses of NovoLog should be infused immediately (within 5-10 minutes) before a meal. Infusion sites should be rotated within the same region to reduce the risk of lipodystrophy. The initial programming of the external insulin infusion pump should be based on the total daily insulin dose of the previous regimen. Although there is significant interpatient variability, approximately 50% of the total dose is usually given as meal-related boluses of NovoLog and the remainder is given as a basal infusion. , Warnings and Precautions (5.8,5.9) How Supplied/Storage and Handling (16.2) Change the NovoLog in the reservoir at least every 6 days, change the infusion sets and the infusion set insertion site at least every 3 days.

The following insulin pumps† have been used in NovoLog clinical or in vitro studies conducted by Novo Nordisk, the manufacturer of NovoLog:

- Medtronic Paradigm® 512 and 712
- MiniMed 508
- Disetronic® D-TRON® and H-TRON®

Before using a different insulin pump with NovoLog, read the pump label to make sure the pump has been evaluated with NovoLog.

2.4 Intravenous Use

NovoLog can be administered intravenously under medical supervision for glycemic control with close monitoring of blood glucose and potassium levels to avoid hypoglycemia and hypokalemia [ ]. For intravenous use, NovoLog should be used at concentrations from 0.05 U/mL to 1.0 U/mL insulin aspart in infusion systems using polypropylene infusion bags. NovoLog has been shown to be stable in infusion fluids such as 0.9% sodium chloride. see , Warnings and Precautions (5) How Supplied/Storage and Handling (16.2)

Inspect NovoLog for particulate matter and discoloration prior to parenteral administration.

3 DOSAGE FORMS AND STRENGTHS

NovoLog is available in the following package sizes: each presentation contains 100 units of insulin aspart per mL (U-100).

- 10 mL vials
- 3 mL PenFill cartridges for the 3 mL PenFill cartridge delivery device (with or without the addition of a NovoPen 3 PenMate) with NovoFine disposable needles ®®®
- 3 mL NovoLog FlexPen
- 3 mL NovoLog FlexTouch

4 CONTRAINDICATIONS

NovoLog is contraindicated

- during episodes of hypoglycemia
- in patients with hypersensitivity to NovoLog or one of its excipients.

5 WARNINGS AND PRECAUTIONS

5.1 Administration

NovoLog has a more rapid onset of action and a shorter duration of activity than regular human insulin. An injection of NovoLog should immediately be followed by a meal within 5-10 minutes. Because of NovoLog’s short duration of action, a longer acting insulin should also be used in patients with type 1 diabetes and may also be needed in patients with type 2 diabetes. Glucose monitoring is recommended for all patients with diabetes and is particularly important for patients using external pump infusion therapy.

Any change of insulin dose should be made cautiously and only under medical supervision. Changing from one insulin product to another or changing the insulin strength may result in the need for a change in dosage. As with all insulin preparations, the time course of NovoLog action may vary in different individuals or at different times in the same individual and is dependent on many conditions, including the site of injection, local blood supply, temperature, and physical activity. Patients who change their level of physical activity or meal plan may require adjustment of insulin dosages. Insulin requirements may be altered during illness, emotional disturbances, or other stresses.

Patients using continuous subcutaneous insulin infusion pump therapy must be trained to administer insulin by injection and have alternate insulin therapy available in case of pump failure.

Needles, NovoLog FlexPen and NovoLog FlexTouch must not be shared.

5.2 Hypoglycemia

Hypoglycemia is the most common adverse effect of all insulin therapies, including NovoLog. Severe hypoglycemia may lead to unconsciousness and/or convulsions and may result in temporary or permanent impairment of brain function or death. Severe hypoglycemia requiring the assistance of another person and/or parenteral glucose infusion or glucagon administration has been observed in clinical trials with insulin, including trials with NovoLog.

The timing of hypoglycemia usually reflects the time-action profile of the administered insulin formulations [ ]. Other factors such as changes in food intake (e.g., amount of food or timing of meals), injection site, exercise, and concomitant medications may also alter the risk of hypoglycemia [ ]. As with all insulins, use caution in patients with hypoglycemia unawareness and in patients who may be predisposed to hypoglycemia (e.g., patients who are fasting or have erratic food intake). The patient’s ability to concentrate and react may be impaired as a result of hypoglycemia. This may present a risk in situations where these abilities are especially important, such as driving or operating other machinery. see Clinical Pharmacology (12) see Drug Interactions (7)

Rapid changes in serum glucose levels may induce symptoms of hypoglycemia in persons with diabetes, regardless of the glucose value. Early warning symptoms of hypoglycemia may be different or less pronounced under certain conditions, such as longstanding diabetes, diabetic nerve disease, use of medications such as beta-blockers, or intensified diabetes control [ ]. These situations may result in severe hypoglycemia (and, possibly, loss of consciousness) prior to the patient’s awareness of hypoglycemia. Intravenously administered insulin has a more rapid onset of action than subcutaneously administered insulin, requiring more close monitoring for hypoglycemia. see Drug Interactions (7)

5.3 Hypokalemia

All insulin products, including NovoLog, cause a shift in potassium from the extracellular to intracellular space, possibly leading to hypokalemia that, if left untreated, may cause respiratory paralysis, ventricular arrhythmia, and death. Use caution in patients who may be at risk for hypokalemia (e.g., patients using potassium-lowering medications, patients taking medications sensitive to serum potassium concentrations, and patients receiving intravenously administered insulin).

5.4 Renal Impairment

As with other insulins, the dose requirements for NovoLog may be reduced in patients with renal impairment [ ]. see Clinical Pharmacology (12.3)

5.5 Hepatic Impairment

As with other insulins, the dose requirements for NovoLog may be reduced in patients with hepatic impairment [ ]. see Clinical Pharmacology (12.3)

5.6 Hypersensitivity and Allergic Reactions

- As with other insulin therapy, patients may experience redness, swelling, or itching at the site of NovoLog injection. These reactions usually resolve in a few days to a few weeks, but in some occasions, may require discontinuation of NovoLog. In some instances, these reactions may be related to factors other than insulin, such as irritants in a skin cleansing agent or poor injection technique. Localized reactions and generalized myalgias have been reported with injected metacresol, which is an excipient in NovoLog. Local Reactions

- Severe, life-threatening, generalized allergy, including anaphylaxis, may occur with any insulin product, including NovoLog. Anaphylactic reactions with NovoLog have been reported post-approval. Generalized allergy to insulin may also cause whole body rash (including pruritus), dyspnea, wheezing, hypotension, tachycardia, or diaphoresis. In controlled clinical trials, allergic reactions were reported in 3 of 735 patients (0.4%) treated with regular human insulin and 10 of 1394 patients (0.7%) treated with NovoLog. In controlled and uncontrolled clinical trials, 3 of 2341 (0.1%) NovoLog-treated patients discontinued due to allergic reactions. Systemic Reactions

5.7 Antibody Production

Increases in anti-insulin antibody titers that react with both human insulin and insulin aspart have been observed in patients treated with NovoLog. Increases in anti-insulin antibodies are observed more frequently with NovoLog than with regular human insulin. Data from a 12-month controlled trial in patients with type 1 diabetes suggest that the increase in these antibodies is transient, and the differences in antibody levels between the regular human insulin and insulin aspart treatment groups observed at 3 and 6 months were no longer evident at 12 months. In this study these antibodies did not appear to cause deterioration in glycemic control or necessitate increases in insulin dose.

In rare cases, the presence of such insulin antibodies may necessitate adjustment of the insulin dose in order to correct a tendency towards hyperglycemia or hypoglycemia.

5.8 Mixing of Insulins

- Mixing NovoLog with NPH human insulin immediately before injection attenuates the peak concentration of NovoLog, without significantly affecting the time to peak concentration or total bioavailability of NovoLog. If NovoLog is mixed with NPH human insulin, NovoLog should be drawn into the syringe first, and the mixture should be injected immediately after mixing.
- The efficacy and safety of mixing NovoLog with insulin preparations produced by other manufacturers have not been studied.
- Insulin mixtures should not be administered intravenously.

5.9 Continuous Subcutaneous Insulin Infusion by External Pump

When using NovoLog in an external insulin pump, the NovoLog-specific information should be followed (e.g., in-use time, frequency of changing infusion sets) because NovoLog-specific information may differ from general pump manual instructions. When used in an external subcutaneous insulin infusion pump, NovoLog should not be mixed with any other insulin or diluent.

Pump or infusion set malfunctions or insulin degradation can lead to a rapid onset of hyperglycemia and ketosis because of the small subcutaneous depot of insulin. This is especially pertinent for rapid-acting insulin analogs that are more rapidly absorbed through skin and have a shorter duration of action. Prompt identification and correction of the cause of hyperglycemia or ketosis is necessary. Interim therapy with subcutaneous injection may be required [ ]. see , , , and Dosage and Administration (2.3) Warnings and Precautions (5.8, 5.9) How Supplied/Storage and Handling (16.2) Patient Counseling Information (17.2)

NovoLog should not be exposed to temperatures greater than 37°C (98.6°F). [ ]. NovoLog that will be used in a pump should not be mixed with other insulin or with a diluentsee , , and Dosage and Administration (2.3) Warnings and Precautions (5.8,5.9), How Supplied/Storage and Handling (16.2) Patient Counseling Information (17.2)

5.10 Fluid retention and heart failure with concomitant use of PPAR-gamma agonists

Thiazolidinediones (TZDs), which are peroxisome proliferator-activated receptor (PPAR)-gamma agonists, can cause dose-related fluid retention, particularly when used in combination with insulin. Fluid retention may lead to or exacerbate heart failure. Patients treated with insulin, including NovoLog, and a PPAR-gamma agonist should be observed for signs and symptoms of heart failure. If heart failure develops, it should be managed according to current standards of care, and discontinuation or dose reduction of the PPAR-gamma agonist must be considered.

6 ADVERSE REACTIONS

Clinical Trial Experience

Because clinical trials are conducted under widely varying designs, the adverse reaction rates reported in one clinical trial may not be easily compared to those rates reported in another clinical trial, and may not reflect the rates actually observed in clinical practice.

- Hypoglycemia

Hypoglycemia is the most commonly observed adverse reaction in patients using insulin, including NovoLog [ ]. see Warnings and Precautions (5)

- Insulin initiation and glucose control intensification

Intensification or rapid improvement in glucose control has been associated with a transitory, reversible ophthalmologic refraction disorder, worsening of diabetic retinopathy, and acute painful peripheral neuropathy. However, long-term glycemic control decreases the risk of diabetic retinopathy and neuropathy.

- Lipodystrophy

Long-term use of insulin, including NovoLog, can cause lipodystrophy at the site of repeated insulin injections or infusion. Lipodystrophy includes lipohypertrophy (thickening of adipose tissue) and lipoatrophy (thinning of adipose tissue), and may affect insulin absorption. Rotate insulin injection or infusion sites within the same region to reduce the risk of lipodystrophy.

- Weight gain

Weight gain can occur with some insulin therapies, including NovoLog, and has been attributed to the anabolic effects of insulin and the decrease in glucosuria.

- Peripheral Edema

Insulin may cause sodium retention and edema, particularly if previously poor metabolic control is improved by intensified insulin therapy.

- Frequencies of adverse drug reactions

The frequencies of adverse drug reactions during NovoLog clinical trials in patients with type 1 diabetes mellitus and type 2 diabetes mellitus are listed in the tables below.

Table 1: Treatment-Emergent Adverse Events in Patients with Type 1 Diabetes Mellitus (Adverse events with frequency ≥ 5% and occurring more frequently with NovoLog compared to human regular insulin are listed)
 | NovoLog + NPH; N= 596 |  | Human Regular Insulin + NPH; N= 286
Preferred Term | N | (%) | N | (%)
Hypoglycemia [Hypoglycemia is defined as an episode of blood glucose concentration <45 mg/dL, with or without symptoms. See Section 14 for the incidence of serious hypoglycemia in the individual clinical trials.] | 448 | 75% | 205 | 72%
Headache | 70 | 12% | 28 | 10%
Injury accidental | 65 | 11% | 29 | 10%
Nausea | 43 | 7% | 13 | 5%
Diarrhea | 28 | 5% | 9 | 3%

Table 2: Treatment-Emergent Adverse Events in Patients with Type 2 Diabetes Mellitus (except for hypoglycemia, adverse events with frequency ≥ 5% and occurring more frequently with NovoLog compared to human regular insulin are listed)
 | NovoLog + NPH; N= 91 |  | Human Regular Insulin + NPH; N= 91
 | N | (%) | N | (%)
Hypoglycemia [Hypoglycemia is defined as an episode of blood glucose concentration <45 mg/dL, with or without symptoms. See Section 14 for the incidence of serious hypoglycemia in the individual clinical trials.] | 25 | 27% | 33 | 36%
Hyporeflexia | 10 | 11% | 6 | 7%
Onychomycosis | 9 | 10% | 5 | 5%
Sensory disturbance | 8 | 9% | 6 | 7%
Urinary tract infection | 7 | 8% | 6 | 7%
Chest pain | 5 | 5% | 3 | 3%
Headache | 5 | 5% | 3 | 3%
Skin disorder | 5 | 5% | 2 | 2%
Abdominal pain | 5 | 5% | 1 | 1%
Sinusitis | 5 | 5% | 1 | 1%

Postmarketing Data

The following additional adverse reactions have been identified during postapproval use of NovoLog. Because these adverse reactions are reported voluntarily from a population of uncertain size, it is generally not possible to reliably estimate their frequency. Medication errors in which other insulins have been accidentally substituted for NovoLog have been identified during postapproval use [ ]. see Patient Counseling Information (17)

7 DRUG INTERACTIONS

A number of substances affect glucose metabolism and may require insulin dose adjustment and particularly close monitoring.

- The following are examples of substances that may increase the blood-glucose-lowering effect and susceptibility to hypoglycemia: oral antidiabetic products, pramlintide, ACE inhibitors, disopyramide, fibrates, fluoxetine, monoamine oxidase (MAO) inhibitors, propoxyphene, salicylates, somatostatin analog (e.g., octreotide), sulfonamide antibiotics.
- The following are examples of substances that may reduce the blood-glucose-lowering effect: corticosteroids, niacin, danazol, diuretics, sympathomimetic agents (e.g., epinephrine, salbutamol, terbutaline), isoniazid, phenothiazine derivatives, somatropin, thyroid hormones, estrogens, progestogens (e.g., in oral contraceptives), atypical antipsychotics.
- Beta-blockers, clonidine, lithium salts, and alcohol may either potentiate or weaken the blood-glucose-lowering effect of insulin.
- Pentamidine may cause hypoglycemia, which may sometimes be followed by hyperglycemia.
- The signs of hypoglycemia may be reduced or absent in patients taking sympatholytic products such as beta-blockers, clonidine, guanethidine, and reserpine.

8 USE IN SPECIFIC POPULATIONS

8.1 Pregnancy

Pregnancy Category B. All pregnancies have a background risk of birth defects, loss, or other adverse outcome regardless of drug exposure. This background risk is increased in pregnancies complicated by hyperglycemia and may be decreased with good metabolic control. It is essential for patients with diabetes or history of gestational diabetes to maintain good metabolic control before conception and throughout pregnancy. Insulin requirements may decrease during the first trimester, generally increase during the second and third trimesters, and rapidly decline after delivery. Careful monitoring of glucose control is essential in these patients. Therefore, female patients should be advised to tell their physician if they intend to become, or if they become pregnant while taking NovoLog.

An open-label, randomized study compared the safety and efficacy of NovoLog (n=157) versus regular human insulin (n=165) in 322 pregnant women with type 1 diabetes. Two-thirds of the enrolled patients were already pregnant when they entered the study. Because only one-third of the patients enrolled before conception, the study was not large enough to evaluate the risk of congenital malformations. Both groups achieved a mean HbA of ~ 6% during pregnancy, and there was no significant difference in the incidence of maternal hypoglycemia.1c

Subcutaneous reproduction and teratology studies have been performed with NovoLog and regular human insulin in rats and rabbits. In these studies, NovoLog was given to female rats before mating, during mating, and throughout pregnancy, and to rabbits during organogenesis. The effects of NovoLog did not differ from those observed with subcutaneous regular human insulin. NovoLog, like human insulin, caused pre- and post-implantation losses and visceral/skeletal abnormalities in rats at a dose of 200 U/kg/day (approximately 32 times the human subcutaneous dose of 1.0 U/kg/day, based on U/body surface area) and in rabbits at a dose of 10 U/kg/day (approximately three times the human subcutaneous dose of 1.0 U/kg/day, based on U/body surface area). The effects are probably secondary to maternal hypoglycemia at high doses. No significant effects were observed in rats at a dose of 50 U/kg/day and in rabbits at a dose of 3 U/kg/day. These doses are approximately 8 times the human subcutaneous dose of 1.0 U/kg/day for rats and equal to the human subcutaneous dose of 1.0 U/kg/day for rabbits, based on U/body surface area.

8.3 Nursing Mothers

It is unknown whether insulin aspart is excreted in human milk. Use of NovoLog is compatible with breastfeeding, but women with diabetes who are lactating may require adjustments of their insulin doses.

8.4 Pediatric Use

NovoLog is approved for use in children for subcutaneous daily injections and for subcutaneous continuous infusion by external insulin pump. NovoLog has not been studied in pediatric patients younger than 2 years of age. NovoLog has not been studied in pediatric patients with type 2 diabetes. Please see for summaries of clinical studies. Section 14 CLINICAL STUDIES

8.5 Geriatric Use

Of the total number of patients (n= 1,375) treated with NovoLog in 3 controlled clinical studies, 2.6% (n=36) were 65 years of age or over. One-half of these patients had type 1 diabetes (18/1285) and the other half had type 2 diabetes (18/90). The HbA response to NovoLog, as compared to human insulin, did not differ by age, particularly in patients with type 2 diabetes. Additional studies in larger populations of patients 65 years of age or over are needed to permit conclusions regarding the safety of NovoLog in elderly compared to younger patients. Pharmacokinetic/pharmacodynamic studies to assess the effect of age on the onset of NovoLog action have not been performed.1c

10 OVERDOSAGE

Excess insulin administration may cause hypoglycemia and, particularly when given intravenously, hypokalemia. Mild episodes of hypoglycemia usually can be treated with oral glucose. Adjustments in drug dosage, meal patterns, or exercise, may be needed. More severe episodes with coma, seizure, or neurologic impairment may be treated with intramuscular/subcutaneous glucagon or concentrated intravenous glucose. Sustained carbohydrate intake and observation may be necessary because hypoglycemia may recur after apparent clinical recovery. Hypokalemia must be corrected appropriately.

11 DESCRIPTION

NovoLog (insulin aspart [rDNA origin] injection) is a rapid-acting human insulin analog used to lower blood glucose. NovoLog is homologous with regular human insulin with the exception of a single substitution of the amino acid proline by aspartic acid in position B28, and is produced by recombinant DNA technology utilizing (baker's yeast). Insulin aspart has the empirical formula C H N 0 S and a molecular weight of 5825.8. Saccharomyces cerevisiae25638165796

Figure 1. Structural formula of insulin aspart.

NovoLog is a sterile, aqueous, clear, and colorless solution, that contains insulin aspart 100 Units/mL, glycerin 16 mg/mL, phenol 1.50 mg/mL, metacresol 1.72 mg/mL, zinc 19.6 mcg/mL, disodium hydrogen phosphate dihydrate 1.25 mg/mL, sodium chloride 0.58 mg/mL and water for injection. NovoLog has a pH of 7.2-7.6. Hydrochloric acid 10% and/or sodium hydroxide 10% may be added to adjust pH.

12 CLINICAL PHARMACOLOGY

12.1 Mechanism of Action

The primary activity of NovoLog is the regulation of glucose metabolism. Insulins, including NovoLog, bind to the insulin receptors on muscle and fat cells and lower blood glucose by facilitating the cellular uptake of glucose and simultaneously inhibiting the output of glucose from the liver.

12.2 Pharmacodynamics

Studies in normal volunteers and patients with diabetes demonstrated that subcutaneous administration of NovoLog has a more rapid onset of action than regular human insulin.

In a study in patients with type 1 diabetes (n=22), the maximum glucose-lowering effect of NovoLog occurred between 1 and 3 hours after subcutaneous injection (see Figure 2). The duration of action for NovoLog is 3 to 5 hours. The time course of action of insulin and insulin analogs such as NovoLog may vary considerably in different individuals or within the same individual. The parameters of NovoLog activity (time of onset, peak time and duration) as designated in Figure 2 should be considered only as general guidelines. The rate of insulin absorption and onset of activity is affected by the site of injection, exercise, and other variables [ ]. see Warnings and Precautions (5.1)

Figure 2. Serial mean serum glucose collected up to 6 hours following a single pre-meal dose of NovoLog (solid curve) or regular human insulin (hatched curve) injected immediately before a meal in 22 patients with type 1 diabetes.

A double-blind, randomized, two-way cross-over study in 16 patients with type 1 diabetes demonstrated that intravenous infusion of NovoLog resulted in a blood glucose profile that was similar to that after intravenous infusion with regular human insulin. NovoLog or human insulin was infused until the patient’s blood glucose decreased to 36 mg/dL, or until the patient demonstrated signs of hypoglycemia (rise in heart rate and onset of sweating), defined as the time of autonomic reaction (R) (see Figure 3).

Figure 3. Mean blood glucose profiles following intravenous infusion of NovoLog (hatched curve) and regular human insulin (solid curve) in 16 patients with type 1 diabetes. R represents the time of autonomic reaction.

12.3 Pharmacokinetics

The single substitution of the amino acid proline with aspartic acid at position B28 in NovoLog reduces the molecule's tendency to form hexamers as observed with regular human insulin. NovoLog is, therefore, more rapidly absorbed after subcutaneous injection compared to regular human insulin.

In a randomized, double-blind, crossover study 17 healthy Caucasian male subjects between 18 and 40 years of age received an intravenous infusion of either NovoLog or regular human insulin at 1.5 mU/kg/min for 120 minutes. The mean insulin clearance was similar for the two groups with mean values of 1.2 l/h/kg for the NovoLog group and 1.2 l/h/kg for the regular human insulin group.

- NovoLog has a faster absorption, a faster onset of action, and a shorter duration of action than regular human insulin after subcutaneous injection (see Figure 2 and Figure 4). The relative bioavailability of NovoLog compared to regular human insulin indicates that the two insulins are absorbed to a similar extent. Bioavailability and Absorption

Figure 4. Serial mean serum free insulin concentration collected up to 6 hours following a single pre-meal dose of NovoLog (solid curve) or regular human insulin (hatched curve) injected immediately before a meal in 22 patients with type 1 diabetes.

In studies in healthy volunteers (total n=107) and patients with type 1 diabetes (total n=40), NovoLog consistently reached peak serum concentrations approximately twice as fast as regular human insulin. The median time to maximum concentration in these trials was 40 to 50 minutes for NovoLog versus 80 to 120 minutes for regular human insulin. In a clinical trial in patients with type 1 diabetes, NovoLog and regular human insulin, both administered subcutaneously at a dose of 0.15 U/kg body weight, reached mean maximum concentrations of 82 and 36 mU/L respectively. Pharmacokinetic/pharmacodynamic characteristics of insulin aspart have not been established in patients with type 2 diabetes. ,

The intra-individual variability in time to maximum serum insulin concentration for healthy male volunteers was significantly less for NovoLog than for regular human insulin. The clinical significance of this observation has not been established.

In a clinical study in healthy non-obese subjects, the pharmacokinetic differences between NovoLog and regular human insulin described above, were observed independent of the site of injection (abdomen, thigh, or upper arm).

- NovoLog has low binding to plasma proteins (<10%), similar to that seen with regular human insulin. After subcutaneous administration in normal male volunteers (n=24), NovoLog was more rapidly eliminated than regular human insulin with an average apparent half-life of 81 minutes compared to 141 minutes for regular human insulin. Distribution and Elimination

Specific Populations

- The pharmacokinetic and pharmacodynamic properties of NovoLog and regular human insulin were evaluated in a single dose study in 18 children (6-12 years, n=9) and adolescents (13-17 years [Tanner grade 2], n=9) with type 1 diabetes. The relative differences in pharmacokinetics and pharmacodynamics in children and adolescents with type 1 diabetes between NovoLog and regular human insulin were similar to those in healthy adult subjects and adults with type 1 diabetes. Children and Adolescents>

- In healthy volunteers, no difference in insulin aspart levels was seen between men and women when body weight differences were taken into account. There was no significant difference in efficacy noted (as assessed by HbA) between genders in a trial in patients with type 1 diabetes. Genderlc

- A single subcutaneous dose of 0.1 U/kg NovoLog was administered in a study of 23 patients with type 1 diabetes and a wide range of body mass index (BMI, 22-39 kg/m). The pharmacokinetic parameters, AUC and C , of NovoLog were generally unaffected by BMI in the different groups – BMI 19-23 kg/m (N=4); BMI 23-27 kg/m (N=7); BMI 27-32 kg/m (N=6) and BMI >32 kg/m (N=6). Clearance of NovoLog was reduced by 28% in patients with BMI >32 kg/m compared to patients with BMI <23 kg/m . Obesity^2max^2^2^2^2^2^2

- Some studies with human insulin have shown increased circulating levels of insulin in patients with renal failure. A single subcutaneous dose of 0.08 U/kg NovoLog was administered in a study to subjects with either normal (N=6) creatinine clearance (CLcr) (> 80 ml/min) or mild (N=7; CLcr = 50-80 ml/min), moderate (N=3; CLcr = 30-50 ml/min) or severe (but not requiring hemodialysis) (N=2; CLcr = <30 ml/min) renal impairment. In this small study, there was no apparent effect of creatinine clearance values on AUC and C of NovoLog. Careful glucose monitoring and dose adjustments of insulin, including NovoLog, may be necessary in patients with renal dysfunction [ ]. Renal Impairmentmax see Warnings and Precautions (5.4)

- Some studies with human insulin have shown increased circulating levels of insulin in patients with liver failure. A single subcutaneous dose of 0.06 U/kg NovoLog was administered in an open-label, single-dose study of 24 subjects (N=6/group) with different degree of hepatic impairment (mild, moderate and severe) having Child-Pugh Scores ranging from 0 (healthy volunteers) to 12 (severe hepatic impairment). In this small study, there was no correlation between the degree of hepatic failure and any NovoLog pharmacokinetic parameter. Careful glucose monitoring and dose adjustments of insulin, including NovoLog, may be necessary in patients with hepatic dysfunction [ ]. Hepatic Impairmentsee Warnings and Precautions (5.5)

The effect of age, ethnic origin, pregnancy and smoking on the pharmacokinetics and pharmacodynamics of NovoLog has not been studied.

13 NONCLINICAL TOXICOLOGY

13.1 Carcinogenesis, Mutagenesis, Impairment of Fertility

Standard 2-year carcinogenicity studies in animals have not been performed to evaluate the carcinogenic potential of NovoLog. In 52-week studies, Sprague-Dawley rats were dosed subcutaneously with NovoLog at 10, 50, and 200 U/kg/day (approximately 2, 8, and 32 times the human subcutaneous dose of 1.0 U/kg/day, based on U/body surface area, respectively). At a dose of 200 U/kg/day, NovoLog increased the incidence of mammary gland tumors in females when compared to untreated controls. The incidence of mammary tumors for NovoLog was not significantly different than for regular human insulin. The relevance of these findings to humans is not known. NovoLog was not genotoxic in the following tests: Ames test, mouse lymphoma cell forward gene mutation test, human peripheral blood lymphocyte chromosome aberration test, micronucleus test in mice, and in UDS test in rat liver hepatocytes. In fertility studies in male and female rats, at subcutaneous doses up to 200 U/kg/day (approximately 32 times the human subcutaneous dose, based on U/body surface area), no direct adverse effects on male and female fertility, or general reproductive performance of animals was observed. in vivoex vivo

13.2 Animal Toxicology and/or Pharmacology

In standard biological assays in mice and rabbits, one unit of NovoLog has the same glucose-lowering effect as one unit of regular human insulin. In humans, the effect of NovoLog is more rapid in onset and of shorter duration, compared to regular human insulin, due to its faster absorption after subcutaneous injection (see Figure 2 and Figure 4). Section 12 CLINICAL PHARMACOLOGY

14 CLINICAL STUDIES

14.1 Subcutaneous Daily Injections

Two six-month, open-label, active-controlled studies were conducted to compare the safety and efficacy of NovoLog to Novolin R in adult patients with type 1 diabetes. Because the two study designs and results were similar, data are shown for only one study (see). NovoLog was administered by subcutaneous injection immediately prior to meals and regular human insulin was administered by subcutaneous injection 30 minutes before meals. NPH insulin was administered as the basal insulin in either single or divided daily doses. Changes in HbA and the incidence rates of severe hypoglycemia (as determined from the number of events requiring intervention from a third party) were comparable for the two treatment regimens in this study () as well as in the other clinical studies that are cited in this section. Diabetic ketoacidosis was not reported in any of the adult studies in either treatment group. Table 31c Table 3

Table 3. Subcutaneous NovoLog Administration in Type 1 Diabetes (24 weeks; n=882)
 | NovoLog + NPH | Novolin R + NPH
N | 596 | 286
Baseline HbA (%)1c [Values are Mean ± SD] | 7.9 ±1.1 | 8.0 ± 1.2
Change from Baseline HbA (%)1c | -0.1 ± 0.8 | 0.0 ± 0.8
Treatment Difference in HbA Mean (95% confidence interval)1c, | -0.2 (-0.3, -0.1)
Baseline insulin dose (IU/kg/24 hours) | 0.7 ± 0.2 | 0.7 ± 0.2
End-of-Study insulin dose (IU/kg/24 hours) | 0.7 ± 0.2 | 0.7 ± 0.2
Patients with severe hypoglycemia (n, %) [Severe hypoglycemia refers to hypoglycemia associated with central nervous system symptoms and requiring the intervention of another person or hospitalization.] | 104 (17%) | 54 (19%)
Baseline body weight (kg); Weight Change from baseline (kg) | 75.3 ± 14.5; 0.5 ± 3.3 | 75.9 ± 13.1; 0.9 ± 2.9

A 24-week, parallel-group study of children and adolescents with type 1 diabetes (n = 283) aged 6 to 18 years compared two subcutaneous multiple-dose treatment regimens: NovoLog (n = 187) or Novolin R (n = 96). NPH insulin was administered as the basal insulin. NovoLog achieved glycemic control comparable to Novolin R, as measured by change in HbA () and both treatment groups had a comparable incidence of hypoglycemia. Subcutaneous administration of NovoLog and regular human insulin have also been compared in children with type 1 diabetes (n=26) aged 2 to 6 years with similar effects on HbA and hypoglycemia.1c Table 41c

Table 4. Pediatric Subcutaneous Administration of NovoLog in Type 1 Diabetes (24 weeks; n=283)
 | NovoLog + NPH | Novolin R + NPH
N | 187 | 96
Baseline HbA (%)1c [Values are Mean ± SD] | 8.3 ± 1.2 | 8.3 ± 1.3
Change from Baseline HbA (%)1c | 0.1± 1.0 | 0.1± 1.1
Treatment Difference in HbA Mean (95% confidence interval)1c, | 0.1 (-0.5, 0.1)
Baseline insulin dose (IU/kg/24 hours) | 0.4 ± 0.2 | 0.6 ± 0.2
End-of-Study insulin dose (IU/kg/24 hours) | 0.4 ± 0.2 | 0.7 ± 0.2
Patients with severe hypoglycemia (n, %) [Severe hypoglycemia refers to hypoglycemia associated with central nervous system symptoms and requiring the intervention of another person or hospitalization.] | 11 (6%) | 9 (9%)
Diabetic ketoacidosis (n, %) | 10 (5%) | 2 (2%)
Baseline body weight (kg); Weight Change from baseline (kg) | 50.6 ± 19.6; 2.7 ± 3.5 | 48.7 ± 15.8; 2.4 ± 2.6

One six-month, open-label, active-controlled study was conducted to compare the safety and efficacy of NovoLog to Novolin R in patients with type 2 diabetes (). NovoLog was administered by subcutaneous injection immediately prior to meals and regular human insulin was administered by subcutaneous injection 30 minutes before meals. NPH insulin was administered as the basal insulin in either single or divided daily doses. Changes in HbA and the rates of severe hypoglycemia (as determined from the number of events requiring intervention from a third party) were comparable for the two treatment regimens. Table 5lc

Table 5. Subcutaneous NovoLog Administration in Type 2 Diabetes (6 months; n=176)
 | NovoLog + NPH | Novolin R + NPH
N | 90 | 86
Baseline HbA (%)1c [Values are Mean ± SD] | 8.1 ± 1.2 | 7.8 ± 1.1
Change from Baseline HbA (%)1c | -0.3 ± 1.0 | -0.1 ± 0.8
Treatment Difference in HbA Mean (95% confidence interval)1c, | - 0.1 (-0.4, -0.1)
Baseline insulin dose (IU/kg/24 hours) | 0.6 ± 0.3 | 0.6 ± 0.3
End-of-Study insulin dose (IU/kg/24 hours) | 0.7 ± 0.3 | 0.7 ± 0.3
Patients with severe hypoglycemia (n, %) [Severe hypoglycemia refers to hypoglycemia associated with central nervous system symptoms and requiring the intervention of another person or hospitalization.] | 9 (10%) | 5 (8%)
Baseline body weight (kg); Weight Change from baseline (kg) | 88.4 ± 13.3; 1.2 ± 3.0 | 85.8 ± 14.8; 0.4 ± 3.1

14.2 Continuous Subcutaneous Insulin Infusion (CSII) by External Pump

Two open-label, parallel design studies (6 weeks [n=29] and 16 weeks [n=118]) compared NovoLog to buffered regular human insulin (Velosulin) in adults with type 1 diabetes receiving a subcutaneous infusion with an external insulin pump. The two treatment regimens had comparable changes in HbA and rates of severe hypoglycemia.1c

Table 6. Adult Insulin Pump Study in Type 1 Diabetes (16 weeks; n=118)
 | NovoLog | Buffered human insulin
N | 59 | 59
Baseline HbA (%)1c [Values are Mean ± SD] | 7.3 ± 0.7 | 7.5 ± 0.8
Change from Baseline HbA (%)1c | 0.0 ± 0.5 | 0.2 ± 0.6
Treatment Difference in HbA Mean (95% confidence interval)1c, | 0.3 (-0.1, 0.4)
Baseline insulin dose (IU/kg/24 hours) | 0.7 ± 0.8 | 0.6 ± 0.2
End-of-Study insulin dose (IU/kg/24 hours) | 0.7 ± 0.7 | 0.6 ± 0.2
Patients with severe hypoglycemia (n, %) [Severe hypoglycemia refers to hypoglycemia associated with central nervous system symptoms and requiring the intervention of another person or hospitalization.] | 1 (2%) | 2 (3%)
Baseline body weight (kg); Weight Change from baseline (kg) | 77.4 ± 16.1; 0.1 ± 3.5 | 74.8 ± 13.8; -0.0 ± 1.7

A randomized, 16-week, open-label, parallel design study of children and adolescents with type 1 diabetes (n=298) aged 4-18 years compared two subcutaneous infusion regimens administered via an external insulin pump: NovoLog (n=198) or insulin lispro (n=100). These two treatments resulted in comparable changes from baseline in HbA and comparable rates of hypoglycemia after 16 weeks of treatment (see).1c Table 7

Table 7. Pediatric Insulin Pump Study in Type 1 Diabetes (16 weeks; n=298)
 | NovoLog | Lispro
N | 198 | 100
Baseline HbA (%)1c [Values are Mean ± SD] | 8.0 ± 0.9 | 8.2 ± 0.8
Change from Baseline HbA (%)1c | -0.1 ± 0.8 | -0.1 ± 0.7
Treatment Difference in HbA Mean (95% confidence interval)1c, | -0.1 (-0.3, 0.1)
Baseline insulin dose (IU/kg/24 hours) | 0.9 ± 0.3 | 0.9 ± 0.3
End-of-Study insulin dose (IU/kg/24 hours) | 0.9 ± 0.2 | 0.9 ± 0.2
Patients with severe hypoglycemia (n, %) [Severe hypoglycemia refers to hypoglycemia associated with central nervous system symptoms and requiring the intervention of another person or hospitalization.] | 19 (10%) | 8 (8%)
Diabetic ketoacidosis (n, %) | 1 (0.5%) | 0 (0)
Baseline body weight (kg); Weight Change from baseline (kg) | 54.1 ± 19.7; 1.8 ± 2.1 | 55.5 ± 19.0; 1.6 ± 2.1

An open-label, 16-week parallel design trial compared pre-prandial NovoLog injection in conjunction with NPH injections to NovoLog administered by continuous subcutaneous infusion in 127 adults with type 2 diabetes. The two treatment groups had similar reductions in HbA and rates of severe hypoglycemia () [ ].1c Table 8 see , , and Indications and Usage (1) Dosage and Administration (2) Warnings and Precautions (5) How Supplied/Storage and Handling (16.2)

Table 8. Pump Therapy in Type 2 Diabetes (16 weeks; n=127)
 | NovoLog pump | NovoLog + NPH
N | 66 | 61
Baseline HbA (%)1c [Values are Mean ± SD] | 8.2 ± 1.4 | 8.0 ± 1.1
Change from Baseline HbA (%)1c | -0.6 ± 1.1 | -0.5 ± 0.9
Treatment Difference in HbA Mean (95% confidence interval)1c, | 0.1 (0.4, 0.3)
Baseline insulin dose (IU/kg/24 hours) | 0.7 ± 0.3 | 0.8 ± 0.5
End-of-Study insulin dose (IU/kg/24 hours) | 0.9 ± 0.4 | 0.9 ± 0.5
Baseline body weight (kg); Weight Change from baseline (kg) | 96.4 ± 17.0; 1.7 ± 3.7 | 96.9 ± 17.9; 0.7 ± 4.1

14.3 Intravenous Administration of NovoLog

See . Section 12.2 CLINICAL PHARMACOLOGY/Pharmacodynamics

16 HOW SUPPLIED/STORAGE AND HANDLING

NDC:64725-0750-1 in a VIAL, GLASS of 10 INJECTION, SOLUTIONS

16.1 How Supplied

NovoLog is available in the following package sizes: each presentation containing 100 Units of insulin aspart per mL (U-100).

10 mL vials | NDC 0169-7501-11
3 mL PenFill cartridges [NovoLog PenFill cartridges are designed for use with Novo Nordisk 3 mL PenFill cartridge compatible insulin delivery devices (with or without the addition of a NovoPen 3 PenMate) with NovoFine disposable needles. FlexPen and FlexTouch can be used with NovoFine or NovoTwist disposable needles.] | NDC 0169-3303-12
3 mL NovoLog FlexPen | NDC 0169-6339-10
3 mL NovoLog FlexTouch | NDC 0169-6338-10

16.2 Recommended Storage

Unused NovoLog should be stored in a refrigerator between 2° and 8°C (36° to 46°F). Do not store in the freezer or directly adjacent to the refrigerator cooling element. NovoLog should not be drawn into a syringe and stored for later use. Do not freeze NovoLog and do not use NovoLog if it has been frozen.

After initial use a vial may be kept at temperatures below 30°C (86°F) for up to 28 days, but should not be exposed to excessive heat or light. Opened vials may be refrigerated. Vials:

Unpunctured vials can be used until the expiration date printed on the label if they are stored in a refrigerator. Keep unused vials in the carton so they will stay clean and protected from light.

PenFill cartridges or NovoLog FlexPen and NovoLog FlexTouch:

Once a cartridge or NovoLog FlexPen or NovoLog FlexTouch is punctured, it should be kept at temperatures below 30°C (86°F) for up to 28 days, but should not be exposed to excessive heat or sunlight. A NovoLog FlexPen or NovoLog FlexTouch or cartridge in use must NOT be stored in the refrigerator. Keep the NovoLog FlexPen or NovoLog FlexTouch and all PenFill cartridges away from direct heat and sunlight. Unpunctured NovoLog FlexPen or NovoLog FlexTouch and PenFill cartridges can be used until the expiration date printed on the label if they are stored in a refrigerator. Keep unused NovoLog FlexPen or NovoLog FlexTouch and PenFill cartridges in the carton so they will stay clean and protected from light.

Always remove the needle after each injection and store the 3 mL PenFill cartridge delivery device or NovoLog FlexPen or NovoLog FlexTouch without a needle attached. This prevents contamination and/or infection, or leakage of insulin, and will ensure accurate dosing. Always use a new needle for each injection to prevent contamination.

Pump:

NovoLog in the pump reservoir should be discarded after at least every 6 days of use or after exposure to temperatures that exceed 37°C (98.6°F). The infusion set and the infusion set insertion site should be changed at least every 3 days.

Summary of Storage Conditions:

The storage conditions are summarized in the following table:

Table 9. Storage conditions for vial, PenFill cartridges, NovoLog FlexPen, and NovoLog FlexTouch
NovoLog; presentation | Room Temperature (below 30°C) Not in-use (unopened) | Refrigerated Not in-use (unopened) | Room Temperature (below 30°C) In-use (opened)
10 mL vial | 28 days | Until expiration date | 28 days (refrigerated/room temperature)
3 mL PenFill cartridges | 28 days | Until expiration date | 28 days; (Do not refrigerate)
3 mL NovoLog FlexPen | 28 days | Until expiration date | 28 days; (Do not refrigerate)
3 mL NovoLog FlexTouch | 28 days | Until expiration date | 28 days; (Do not refrigerate)

Storage of Diluted NovoLog

NovoLog diluted with Insulin Diluting Medium for NovoLog to a concentration equivalent to U-10 or equivalent to U-50 may remain in patient use at temperatures below 30°C (86°F) for 28 days.

Storage of NovoLog in Infusion Fluids

Infusion bags prepared as indicated under are stable at room temperature for 24 hours. Some insulin will be initially adsorbed to the material of the infusion bag. Dosage and Administration (2)

17 PATIENT COUNSELING INFORMATION

[See ] FDA Approved Patient Labeling (17.3)

17.1 Physician Instructions

Maintenance of normal or near-normal glucose control is a treatment goal in diabetes mellitus and has been associated with a reduction in diabetic complications. Patients should be informed about potential risks and benefits of NovoLog therapy including the possible adverse reactions. Patients should also be offered continued education and advice on insulin therapies, injection technique, life-style management, regular glucose monitoring, periodic glycosylated hemoglobin testing, recognition and management of hypo- and hyperglycemia, adherence to meal planning, complications of insulin therapy, timing of dose, instruction in the use of injection or subcutaneous infusion devices, and proper storage of insulin. Patients should be informed that frequent, patient-performed blood glucose measurements are needed to achieve optimal glycemic control and avoid both hyper- and hypoglycemia.

Patients should receive proper training on how to use NovoLog. Instruct patients that when injecting NovoLog, they must press and hold down the dose button until the dose counter shows 0 and then keep the needle in the skin and count slowly to 6. When the dose counter returns to 0, the prescribed dose is not completely delivered until 6 seconds later. If the needle is removed earlier, they may see a stream of insulin coming from the needle tip. If so, the full dose will not be delivered (a possible under-dose may occur by as much as 20%), and they should increase the frequency of checking their blood glucose levels and possible additional insulin administration may be necessary.

- If 0 does not appear in the dose counter after continuously pressing the dose button, the patient may have used a blocked needle. In this case they would have received insulin – even though the dose counter has moved from the original dose that was set. notany
- If the patient did have a blocked needle, instruct them to change the needle as described in Section 5 of the Instructions for Use and repeat all steps in the IFU starting with Section 1: Prepare your pen with a new needle. Make sure the patient selects the full dose needed.

The patient’s ability to concentrate and react may be impaired as a result of hypoglycemia. This may present a risk in situations where these abilities are especially important, such as driving or operating other machinery. Patients who have frequent hypoglycemia or reduced or absent warning signs of hypoglycemia should be advised to use caution when driving or operating machinery.

Accidental substitutions between NovoLog and other insulin products have been reported. Patients should be instructed to always carefully check that they are administering the appropriate insulin to avoid medication errors between NovoLog and any other insulin. The written prescription for NovoLog should be written clearly, to avoid confusion with other insulin products, for example, NovoLog Mix 70/30.

17.2 Patients Using Pumps

Patients using external pump infusion therapy should be trained in intensive insulin therapy with multiple injections and in the function of their pump and pump accessories.

The following insulin pumps† have been used in NovoLog clinical or studies conducted by Novo Nordisk, the manufacturer of NovoLog: in vitro

- Medtronic Paradigm 512 and 712 ®
- MiniMed 508
- Disetronic D-TRON and H-TRON ®®®

Before using another insulin pump with NovoLog, read the pump label to make sure the pump has been evaluated with NovoLog.

NovoLog is recommended for use in any reservoir and infusion sets that are compatible with insulin and the specific pump. Please see recommended reservoir and infusion sets in the pump manual.

To avoid insulin degradation, infusion set occlusion, and loss of the preservative (metacresol), insulin in the reservoir should be replaced at least every 6 days; infusion sets and infusion set insertion sites should be changed at least every 3 days.

° ° The temperature of the insulin may exceed ambient temperature when the pump housing, cover, tubing, or sport case is exposed to sunlight or radiant heat. Infusion sites that are erythematous, pruritic, or thickened should be reported to medical personnel, and a new site selected because continued infusion may increase the skin reaction and/or alter the absorption of NovoLog. Pump or infusion set malfunctions or insulin degradation can lead to hyperglycemia and ketosis in a short time because of the small subcutaneous depot of insulin. This is especially pertinent for rapid-acting insulin analogs that are more rapidly absorbed through skin and have shorter duration of action. These differences are particularly relevant when patients are switched from multiple injection therapy. Prompt identification and correction of the cause of hyperglycemia or ketosis is necessary. Problems include pump malfunction, infusion set occlusion, leakage, disconnection or kinking, and degraded insulin. Less commonly, hypoglycemia from pump malfunction may occur. If these problems cannot be promptly corrected, patients should resume therapy with subcutaneous insulin injection and contact their physician [ ]. Insulin exposed to temperatures higher than 37 C (98.6 F) should be discarded. see , and Dosage and Administration (2) Warnings and Precautions (5) How Supplied/Storage and Handling (16.2)

17.3 FDA Approved Patient Labeling

See separate leaflet.

Rx only

Date of Issue: April 25, 2014

Version: 22

Novo Nordisk , NovoLog , NovoPen 3, PenFill , Novolin , FlexPen , FlexTouch , PenMate , NovoFine and NovoTwist are registered trademarks of Novo Nordisk A/S.®®®®®®®®®®

NovoLog is covered by US Patent Nos. 5,618,913, 5,866,538, and other patents pending.®

FlexPen is covered by US Patent Nos. RE 41,956, 6,004,297, RE 43,834, and other patents pending.®

FlexTouch pen is covered by US Patent Nos. 7,686,786, 6,899,699, and other patents pending.®

PenFill is covered by US Patent No. 5,693,027.®

†The brands listed are the registered trademarks of their respective owners and are not trademarks of Novo Nordisk A/S.

© 2002-2014 Novo Nordisk

Manufactured by:

Novo Nordisk A/S

DK-2880 Bagsvaerd, Denmark

For information about NovoLog contact:

Novo Nordisk Inc.

800 Scudders Mill Road

Plainsboro, New Jersey 08536

1-800-727-6500

www.novonordisk-us.com

PATIENT INFORMATION

NovoLog (NŌ-vō-log)®

(insulin aspart [rDNA origin] injection)

What is NovoLog?

- NovoLog is a man-made insulin that is used to control high blood sugar in adults and children with diabetes mellitus.

Who should not take NovoLog?

Do not take NovoLog if you:

- are having an episode of low blood sugar (hypoglycemia).
- have an allergy to NovoLog or any of the ingredients in NovoLog.

Before taking NovoLog, tell your healthcare provider about all your medical conditions including, if you are:

- pregnant, planning to become pregnant, or are breastfeeding.
- taking new prescription or over-the-counter medicines, vitamins, or herbal supplements.

Before you start taking NovoLog, talk to your healthcare provider about low blood sugar and how to manage it.

How should I take NovoLog?

- that come with your NovoLog. Read theInstructions for Use
- Take NovoLog exactly as your healthcare provider tells you to.
- You should eat a meal within 5 to 10 minutes after you take your dose of NovoLog. NovoLog starts acting fast.
- Know the type and strength of insulin you take. change the type of insulin you take unless your healthcare provider tells you to. The amount of insulin and the best time for you to take your insulin may need to change if you take different types of insulin. Do not
- Ask your healthcare provider what your blood sugars should be and when you should check your blood sugar levels. Check your blood sugar levels.
- You may give another person an infection or get an infection from them. Do not share your NovoLog FlexPen, FlexTouch or needles with another person.

What should I avoid while taking NovoLog?

While taking NovoLog do not:

- Drive or operate heavy machinery, until you know how NovoLog affects you.
- Drink alcohol or use prescription or over-the-counter medicines that contain alcohol.

What are the possible side effects of NovoLog?

NovoLog may cause serious side effects that can lead to death, including:

Signs and symptoms that may indicate low blood sugar include: Low blood sugar (hypoglycemia).

- dizziness or light-headedness
- blurred vision
- anxiety, irritability, or mood changes
- sweating
- slurred speech
- hunger
- confusion
- shakiness
- headache
- fast heart beat

Your insulin dose may need to change because of:

- change in level of physical activity or exercise
- increased stress
- change in diet
- weight gain or loss
- illness

Other common side effects of NovoLog may include:

- low potassium in your blood (hypokalemia), reactions at the injection site, itching, rash, serious allergic reactions (whole body reactions), skin thickening or pits at the injection site (lipodystrophy), weight gain, and swelling of your hands and feet.

Get emergency medical help if you have:

- trouble breathing, shortness of breath, fast heartbeat, swelling of your face, tongue, or throat, sweating, extreme drowsiness, dizziness, confusion.

These are not all the possible side effects of NovoLog. Call your doctor for medical advice about side effects. You may report side effects to FDA at 1-800-FDA-1088.

General information about the safe and effective use of NovoLog.

Medicines are sometimes prescribed for purposes other than those listed in a Patient Information leaflet. You can ask your pharmacist or healthcare provider for information about NovoLog that is written for health professionals. Do not use NovoLog for a condition for which it was not prescribed. Do not give NovoLog to other people, even if they have the same symptoms that you have. It may harm them.

What are the ingredients in NovoLog?

insulin aspart (rDNA origin) Active Ingredient:

glycerin, phenol, metacresol, zinc, disodium hydrogen phosphate dihydrate, sodium chloride and water for injection Inactive Ingredients:

Manufactured by:

Novo Nordisk A/S

DK-2880 Bagsvaerd, Denmark

For more information, go to www.novonordisk-us.com or call 1-800-727-6500.

This Patient Information has been approved by the U.S. Food and Drug Administration

Revised: 10/2013

For more information go to

www.novologflextouch.com

© 2002-2013 Novo Nordisk

PATIENT INSTRUCTIONS FOR USE

NovoLog (NŌ-vō-log)®

(insulin aspart [rDNA origin] injection)

10 mL vial (100 Units/mL, U-100)

Read this Instructions for Use before you start taking NovoLog and each time you get a refill. There may be new information. This information does not take the place of talking to your healthcare provider about your medical condition or your treatment. ®

Supplies you will need to give your NovoLog injection:®

- 10 mL NovoLog vial ®
- insulin syringe and needle
- alcohol swab

Preparing your NovoLog dose:®

- Wash your hands with soap and water.
- Before you start to prepare your injection, check the NovoLog label to make sure that you are taking the right type of insulin. This is especially important if you use more than 1 type of insulin. ®
- NovoLog should look clear and colorless. use NovoLog if it is thick, cloudy, or is colored. ® Do not®
- use NovoLog past the expiration date printed on the label. Do not®

Pull off the tamper resistant cap (See Figure A). Step 1:

Wipe the rubber stopper with an alcohol swab (See Figure B). Step 2:

Hold the syringe with the needle pointing up.Pull down on the plunger until the black tip reaches the line for the number of units for your prescribed dose (See Figure C). Step 3:

Push the needle through the rubber stopper of the NovoLog vial (See Figure D). Step 4:®

Push the plunger all the way in. This puts air into the NovoLog vial (See Figure E). Step 5:®

Turn the NovoLog vial and syringe upside down and slowly pull the plunger down until the black tip is a few units past the line for your dose (See Figure F). Step 6:®

- If there are air bubbles, tap the syringe gently a few times to let any air bubbles rise to the top (See Figure G).

Slowly push the plunger up until the black tip reaches the line for your NovoLog dose (See Figure H). Step 7:®

Check the syringe to make sure you have the right dose of NovoLog . Step 8:®

Pull the syringe out of the vial’s rubber stopper (See Figure I). Step 9:

Giving your Injection:

- Inject your NovoLog exactly as your healthcare provider has shown you. Your healthcare provider should tell you if you need to pinch the skin before injecting. ®
- NovoLog can be injected under the skin (subcutaneously) of your stomach area, buttocks, upper legs or upper arms, infused in an insulin pump, or given through a needle in your arm (intravenously) by your healthcare provider. ®
- If you inject NovoLog ,change (rotate) your injection sites within the area you choose for each dose. use the same injection site for each injection. ® Do not
- If you use NovoLog in an insulin pump, you should change your insertion site every 3 days. The insulin in the reservoir should be changed at least every 6 days even if you have not used all of the insulin. ®
- If you use NovoLog in an insulin pump, see your insulin pump manual for instructions or talk to your healthcare provider. ®
- NPH insulin is the only type of insulin that can be mixed with NovoLog . mix NovoLog with any other type of insulin. ® Do not®
- NovoLog should be mixed with NPH insulin if it is going to be injected right away under your skin (subcutaneously). ® only
- NovoLog should be drawn up into the syringe you draw up your NPH insulin. ® before
- Talk to your healthcare provider if you are not sure about the right way to mix NovoLog and NPH insulin. ®

Choose your injection site and wipe the skin with an alcohol swab. Let the injection site dry before you inject your dose (See Figure J). Step 10:

Insert the needle into your skin. Push down on the plunger to inject your dose (See Figure K). Step 11: Needle should remain in the skin for at least 6 seconds to make sure you have injected all the insulin.

Pull the needle out of your skin. After that, you may see a drop of NovoLog at the needle tip. This is normal and does not affect the dose you just received (See Figure L). Step 12:®

- If you see blood after you take the needle out of your skin, press the injection site lightly with a
piece of gauze or an alcohol swab. rub the area. Do not

After your injection:

- recap the needle. Recapping the needle can lead to a needle stick injury. Do not
- Throw away empty insulin vials, used syringes, and needles in a sharps container or some type of hard plastic or metal container with a screw on cap such as a detergent bottle or empty coffee can. Check with your healthcare provider about the right way to throw away the container. There may be local or state laws about how to throw away used syringes and needles. Do not throw away used syringes and needles in household trash or recycling bins.

How should I store NovoLog ?®

freeze NovoLog . use NovoLog if it has been frozen. Do not® Do not®

- Keep NovoLog away from heat or light. ®
- Store opened and unopened NovoLog vials in the refrigerator at 36 F to 46 F (2 C to 8 C). Opened NovoLog vials can also be stored out of the refrigerator below 86 F (30 C). ®OOOO®OO
- Unopened vials may be used until the expiration date printed on the label, if they are kept in the refrigerator.
- Opened NovoLog vials should be thrown away after 28 days, even if they still have insulin left in them. ®

General information about the safe and effective use of NovoLog®

- Always use a new syringe and needle for each injection.
- Do not share syringes or needles.
- Keep NovoLog vials, syringes, and needles out of the reach of children. ®

This Instructions for Use has been approved by the U.S. Food and Drug Administration.

Manufactured by:

Novo Nordisk A/S

DK-2880 Bagsvaerd, Denmark

. NovoLog is a registered trademark of Novo Nordisk A/S®

NovoLog is covered by US Patent Nos. 5,618,913, 5,866,538, and other patents pending.®

© 2002-2013 Novo Nordisk

For information about NovoLog contact:®

Novo Nordisk Inc.

800 Scudders Mill Road

Plainsboro, New Jersey 08536

1-800-727-6500

www.novonordisk-us.com

Revised: March 2013

PATIENT INSTRUCTIONS FOR USE

NovoLog® 3 mL PenFill cartridge (100 Units/mL, U-100)®

Before using the NovoLog cartridge®

1. Talk with your healthcare provider for information about where to inject NovoLog (injection sites) and how to give an injection with your insulin delivery device. ®
2. Read the instruction manual that comes with your insulin delivery device for complete instructions on how to use the PenFill cartridge with the device. ®

How to use the NovoLog cartridge®

1. Just before using your NovoLog cartridge, check to make sure that you have the right type of insulin. This is especially important if you use different types of insulin. Check your insulin.®
2. The insulin should be clear and colorless. The tamper-resistant foil should be in place before the first use. If the foil has been broken or removed before your first use of the cartridge, or if the insulin is cloudy or colored, do not use it. Call Novo Nordisk at 1-800-727-6500. Carefully look at the cartridge and the insulin inside it.
3. well with soap and water. If you clean your injection site with an alcohol swab, let the injection site dry before you inject. Talk with your healthcare provider for guidance on injection sites and how to give an injection with your insulin delivery device. Wash your hands
4. Gather your supplies for injecting NovoLog . ®
5. Insert a 3 mL cartridge into your Novo Nordisk 3 mL PenFill cartridge compatible insulin delivery device. Wipe the front rubber stopper of the 3 mL PenFill cartridge with an alcohol swab, then attach a new needle. For NovoFine needles, remove the big outer needle cap and the inner needle cap. Always use a new needle for each injection to prevent infection. ®®®

Giving the airshot before each injection:

To prevent the injection of air and to make sure insulin is delivered, you must do an airshot before each injection. Hold the device with the needle pointing up and gently tap the PenFill cartridge holder with your finger a few times to raise any air bubbles to the top of the cartridge. Do the airshot as described in the device instruction manual.®

Giving the injection

6. Dial the number of units on the insulin delivery device that you need to inject. Inject the right way as shown to you by your healthcare provider.

7. Insert the needle into the skin. Inject the dose by pressing the push button all the way in. Keep the needle in the skin for at least 6 seconds, and keep the push button pressed all the way in until the needle has been pulled out from the skin. This will make sure that the full dose has been given. You may see a drop of NovoLog at the needle tip. This is normal and has no effect on the dose you just received. If blood appears after you take the needle out of your skin, press the injection site lightly with a finger.® Do not rub the area.

After the injection

8. Recapping can lead to a needle stick injury. Do not recap the needle.

9. Remove the needle from the PenFill cartridge after each injection. Keep the 3 mL PenFill cartridge in the insulin delivery device. The needle should not be attached to the 3 mL PenFill cartridge during storage. This will prevent infection or leakage of insulin and will help ensure that you receive the right dose of NovoLog .®®®®

10. Put the used needle and cartridge in a sharps container, or some type of hard plastic or metal container with a screw on top such as a detergent bottle or coffee can. Check with your healthcare provider about the right way to throw away used needles and cartridges. There may be local or state laws about how to throw away used needles and syringes. Do not throw used needles and cartridges in household trash or recycling bins.

11. Put the pen cap back on the Novo Nordisk 3 mL PenFill cartridge compatible insulin delivery device.®

Date of Issue: March 2013

Version: 9

Novo Nordisk , NovoLog , PenFill , and NovoFine are registered trademarks of Novo Nordisk A/S.®®®®

NovoLog is covered by US Patent Nos. 5,618,913, 5,866,538, and other patents pending.®

PenFill is covered by US Patent No. 5,693,027.®

© 2002-2013 Novo Nordisk

Manufactured by:

Novo Nordisk A/S

DK-2880 Bagsvaerd, Denmark

For information about NovoLog contact:®

Novo Nordisk Inc.

800 Scudders Mill Road

Plainsboro, New Jersey 08536

PATIENT INSTRUCTIONS FOR USE

NovoLog (NŌ-vō-log)FlexTouch Pen®®

(insulin aspart [rDNA origin] injection)

- containing 300 units of U-100 NovoLog (insulin aspart [rDNA origin] injection) insulin. You can inject from 1 to 80 units in a single injection. NovoLog FlexTouch Pen (“Pen”) is a prefilled disposable pen
- Do not share your NovoLog FlexTouch Pen with another person. You may give an infection to them or get an infection from them.
- This Pen is not recommended for use by the blind or visually impaired without the assistance of a person trained in the proper use of the product.

Supplies you will need to give your NovoLog injection:

- NovoLog FlexTouch Pen
- a new NovoFine or NovoTwist needle
- alcohol swab
- 1 sharps container for throwing away used Pens and needles. See “Disposing of used NovoLog FlexTouch Pens and needles” at the end of these instructions.

Preparing your NovoLog FlexTouch Pen:

- Wash your hands with soap and water.
- Before you start to prepare your injection, check the NovoLog FlexTouch Pen label to make sure you are taking the right type of insulin. This is especially important if you take more than 1 type of insulin.
- NovoLog should look clear and colorless. use NovoLog if it is thick, cloudy, or is colored. Do not
- use NovoLog past the expiration date printed on the label or 28 days after you start using the Pen. Do not
- Always use a new needle for each injection to help ensure sterility and prevent blocked needles.

Step 1:

- Pull Pen cap straight off (See Figure B).

(Figure B)

Step 2:

- (See Figure C). NovoLog should look clear and colorless. use it if it looks cloudy or colored. Check the liquid in the Pen Do not

(Figure C)

Step 3:

- Select a new needle.
- Pull off the paper tab from the outer needle cap (See Figure D).

(Figure D)

Step 4:

- Push the capped needle straight onto the Pen and twist the needle on until it is tight (See Figure E).

(Figure E)

Step 5:

- Pull off the outer needle cap. throw it away (See Figure F). Do not

(Figure F)

Step 6:

- Pull off the inner needle cap and throw it away (See Figure G).

(Figure G)

Priming your NovoLog FlexTouch Pen:

Step 7:

- Turn the dose selector to (See Figure H). select 2 units

(Figure H)

Step 8:

- Hold the Pen with the needle pointing up. Tap the top of the Pen gently a few times to let any air bubbles rise to the top (See Figure I).

(Figure I)

Step 9:

- Press and hold in the dose button until the dose counter shows “0”. The “0” must line up with the dose pointer. Hold the Pen with the needle pointing up.
- A drop of insulin should be seen at the needle tip (See Figure J).
  - If you see a drop of insulin, repeat steps 7 to 9, no more than 6 times. do not
  - If you see a drop of insulin, change the needle and repeat steps 7 to 9. still do not

(Figure J)

Selecting your dose:

Step 10:

- The dose pointer should line up with your dose (See Figure K). Turn the dose selector to select the number of units you need to inject.
  - If you select the wrong dose, you can turn the dose selector forwards or backwards to the correct dose.
  - The numbers are printed on the dial. even
  - The numbers are shown as lines. odd

(Figure K)

- The NovoLog FlexTouch Pen insulin scale will show you how much insulin is left in your Pen (See Figure L).
- To see how much insulin is left in your NovoLog FlexTouch Pen:
  - Turn the dose selector until it stops. The dose counter will line up with the number of units of insulin that is left in your Pen. If the dose counter shows 80, there are units left in your Pen. at least 80
  - If the dose counter shows the number shown in the dose counter is the number of units left in your Pen. less than 80,

(Figure L)

Giving your injection:

- Inject your NovoLog exactly as your healthcare provider has shown you. Your healthcare provider should tell you if you need to pinch the skin before injecting.
- NovoLog can be injected under the skin (subcutaneously) of your stomach area (abdomen), buttocks, upper legs (thighs) or upper arms.
- Change (rotate) your injection sites within the area you choose for each dose. use the same injection site for each injection. Do not

Step 11:

- Choose your injection site and wipe the skin with an alcohol swab. Let the injection site dry before you inject your dose (See Figure M).

(Figure M)

Step 12:

- (See Figure N). Insert the needle into your skin
  - cover it with your fingers, this can stop your injection. Make sure you can see the dose counter. Do not

(Figure N)

Step 13:

- (See Figure O). Press and hold down the dose button until the dose counter shows “0”
  - The “0” must line up with the dose pointer. You may then hear or feel a click.

(Figure O)

- the dose counter has returned to “0” and (See Figure P). Keep the needle in your skin afterslowly count to 6

(Figure P)

  - When the dose counter returns to “0”, you will not get your full dose until 6 seconds later.
  - If the needle is removed before you count to 6, you may see a stream of insulin coming from the needle tip.
  - If you see a stream of insulin coming from the needle tip you will not get your full dose. If this happens you should check your blood sugar levels more often because you may need more insulin.

Step 14:

- (See Figure Q). Pull the needle out of your skin
  - If you see blood after you take the needle out of your skin, press the injection site lightly with a piece of gauze or an alcohol swab. rub the area. Do not

(Figure Q)

Step 15:

- (See Figure R). Carefully remove the needle from the Pen and throw it away
  - recap the needle. Recapping the needle can lead to needle stick injury. Do not

(Figure R)

- If you have a sharps container, carefully slip the needle into the outer needle cap (See Figure S). Safely remove the needle and throw it away as soon as you can. do not

(Figure S)

  - store the Pen with the needle attached. Storing without the needle attached helps prevent leaking, blocking of the needle, and air from entering the Pen. Do not

Step 16:

- Replace the Pen cap by pushing it straight on (See Figure T).

(Figure T)

After your injection:

- Put your used NovoLog FlexTouch Pen and needles in a FDA-cleared sharps disposal container right away after use. Do not throw away (dispose of) loose needles and Pens in your household trash.
- If you do not have a FDA-cleared sharps disposal container, you may use a household container that is:
  - made of a heavy-duty plastic
  - can be closed with a tight-fitting, puncture-resistant lid, without sharps being able to come out
  - upright and stable during use
  - leak-resistant
  - properly labeled to warn of hazardous waste inside the container
- When your sharps disposal container is almost full, you will need to follow your community guidelines for the right way to dispose of your sharps disposal container. There may be state or local laws about how you should throw away used needles and syringes. For more information about the safe sharps disposal, and for specific information about sharps disposal in the state that you live in, go to the FDA’s website at: . http://www.fda.gov/safesharpsdisposal
- Do not dispose of your used sharps disposal container in your household trash unless your community guidelines permit this. Do not recycle your used sharps disposal container.

How should I store my NovoLog FlexTouch Pen?

- Store unused NovoLog FlexTouch Pens in the refrigerator at 36°F to 46°F (2°C to 8°C).
- Store the Pen you are currently using out of the refrigerator below 86°F.
- freeze NovoLog. use NovoLog if it has been frozen. Do not Do not
- Keep NovoLog away from heat or light.
- Unused Pens may be used until the expiration date printed on the label, if kept in the refrigerator.
- The NovoLog FlexTouch Pen you are using should be thrown away after 28 days, even if it still has insulin left in it.

General Information about the safe and effective use of NovoLog.

- Keep NovoLog FlexTouch Pens and needles out of the reach of children.
- use a new needle for each injection. Always
- share Pens or needles. Do not

This Instructions for Use has been approved by the U.S. Food and Drug Administration.

Manufactured By:

Novo Nordisk A/S

DK-2880 Bagsvaerd, Denmark

Revised: 10/2013

PATIENT INSTRUCTIONS FOR USE

NovoLog FlexPen®®

Introduction

Please read the following instructions carefully before using your NovoLog FlexPen .®®

NovoLog FlexPen is a disposable dial-a-dose insulin pen. You can select doses from 1 to 60 units in increments of 1 unit. NovoLog FlexPen is designed to be used with NovoFine needles.®

NovoLog FlexPen should not be used by people who are blind or have severe visual problems without the help of a person who has good eyesight and who is trained to use the NovoLog FlexPen the right way. Δ

Getting ready

Make sure you have the following items:

- NovoLog FlexPen
- New NovoFine needle
- Alcohol swab

Preparing Your NovoLog FlexPen

Wash your hands with soap and water. Before you start to prepare your injection, check the label to make sure that you are taking the right type of insulin. This is especially important if you take more than 1 type of insulin. NovoLog should look clear.

. Pull off the pen cap (see diagram A). A

Wipe the rubber stopper with an alcohol swab.

B. Attaching the needle

Remove the protective tab from a disposable needle.

Screw the needle tightly onto your FlexPen. It is important that the needle is put on straight (see diagram B).

Never place a disposable needle on your NovoLog FlexPen until you are ready to take your injection.

Pull off the big outer needle cap (see diagram C). C.

Pull off the inner needle cap and dispose of it (see diagram D). D.

Always use a new needle for each injection to help ensure sterility and prevent blocked needles. Δ
Be careful not to bend or damage the needle before use. Δ
To reduce the risk of unexpected needle sticks, never put the inner needle cap back on the needle. Δ

Giving the airshot before each injection

Before each injection small amounts of air may collect in the cartridge during normal use. To avoid injecting air and to ensure proper dosing:

Turn the dose selector to select 2 units (see diagram E). E.

Hold your NovoLog FlexPen with the needle pointing up. Tap the cartridge gently with your finger a few times to make any air bubbles collect at the top of the cartridge (see diagram F). F.

Keep the needle pointing upwards, press the push-button all the way in (see diagram G). The dose selector returns to 0. G.

A drop of insulin should appear at the needle tip. If not, change the needle and repeat the procedure no more than 6 times.

If you do not see a drop of insulin after 6 times, do not use the NovoLog FlexPen and contact Novo Nordisk at 1-800-727-6500.

A small air bubble may remain at the needle tip, but it will not be injected.

Selecting your dose

Check and make sure that the dose selector is set at 0.

Turn the dose selector to the number of units you need to inject. The pointer should line up with your dose. H.

The dose can be corrected either up or down by turning the dose selector in either direction until the correct dose lines up with the pointer (see diagram H). When turning the dose selector, be careful not to press the push-button as insulin will come out.

You cannot select a dose larger than the number of units left in the cartridge.

You will hear a click for every single unit dialed. Do not set the dose by counting the number of clicks you hear.

Δ Do not use the cartridge scale printed on the cartridge to measure your dose of insulin.

Giving the injection

Do the injection exactly as shown to you by your healthcare provider. Your healthcare provider should tell you if you need to pinch the skin before injecting.

Insert the needle into your skin. I.

Inject the dose by pressing the push-button all the way in until the 0 lines up with the pointer (see diagram I). Be careful only to push the button when injecting.

Turning the dose selector will not inject insulin.

Keep the needle in the skin for at least 6 seconds, and keep the push-button pressed all the way in until the needle has been pulled out from the skin (see diagram J). This will make sure that the full dose has been given. J.

You may see a drop of NovoLog at the needle tip. This is normal and has no effect on the dose you just received. If blood appears after you take the needle out of your skin, press the injection site lightly with a finger. Do not rub the area.

After the injection

Recapping can lead to a needle stick injury. Remove the needle from the NovoLog FlexPen after each injection. This helps to prevent infection, leakage of insulin, and will help to make sure you inject the right dose of insulin. Do not recap the needle.

Put the needle and any empty NovoLog FlexPen or any used NovoLog FlexPen still containing insulin in a sharps container or some type of hard plastic or metal container with a screw top such as a detergent bottle or empty coffee can. These containers should be sealed and thrown away the right way. Check with your healthcare provider about the right way to throw away used syringes and needles. There may be local or state laws about how to throw away used needles and syringes. Do not throw away used needles and syringes in household trash or recycling bins. Δ

The NovoLog FlexPen prevents the cartridge from being completely emptied. It is designed to deliver 300 units.

. Put the pen cap on the NovoLog FlexPen and store the NovoLog FlexPen without the needle attached (see diagram K). K

L Function Check

If your NovoLog FlexPen is not working the right way, follow the steps below:

- Screw on a new NovoFine needle.
- Remove the big outer needle cap and the inner needle cap.
- Do an airshot as described in "Giving the airshot before each injection".
- Put the big outer needle cap onto the needle. Do not put on the inner needle cap.
- Turn the dose selector so the dose indicator window shows 20 units.
- Hold the NovoLog FlexPen so the needle is pointing down.
- Press the push-button all the way in.

The insulin should fill the lower part of the big outer needle cap (see diagram L). If the NovoLog FlexPen has released too much or too little insulin, do the function check again. If the same problem happens again, do not use your NovoLog FlexPen and contact Novo Nordisk at 1-800-727-6500.

Maintenance

Your FlexPen is designed to work accurately and safely. It must be handled with care. Avoid dropping your FlexPen as it may damage it. If you are concerned that your FlexPen is damaged, use a new one. You can clean the outside of your FlexPen by wiping it with a damp cloth. Do not soak or wash your FlexPen as it may damage it. Do not refill your FlexPen.

Remove the needle from the NovoLog FlexPen after each injection. This helps to ensure sterility, prevent leakage of insulin, and will help to make sure you inject the right dose of insulin for future injections. Δ

Be careful when handling used needles to avoid needle sticks and transfer of infectious diseases. Δ

Keep your NovoLog FlexPen and needles out of the reach of children. Δ

Use NovoLog FlexPen as directed to treat your diabetes. Needles and NovoLog FlexPen must not be shared. Δ

Always use a new needle for each injection. Δ

Novo Nordisk is not responsible for harm due to using this insulin pen with products not recommended by Novo Nordisk. Δ

As a precautionary measure, always carry a spare insulin delivery device in case your NovoLog FlexPen is lost or damaged. Δ

Remember to keep the disposable NovoLog FlexPen with you. Do not leave it in a car or other location where it can get too hot or too cold. Δ